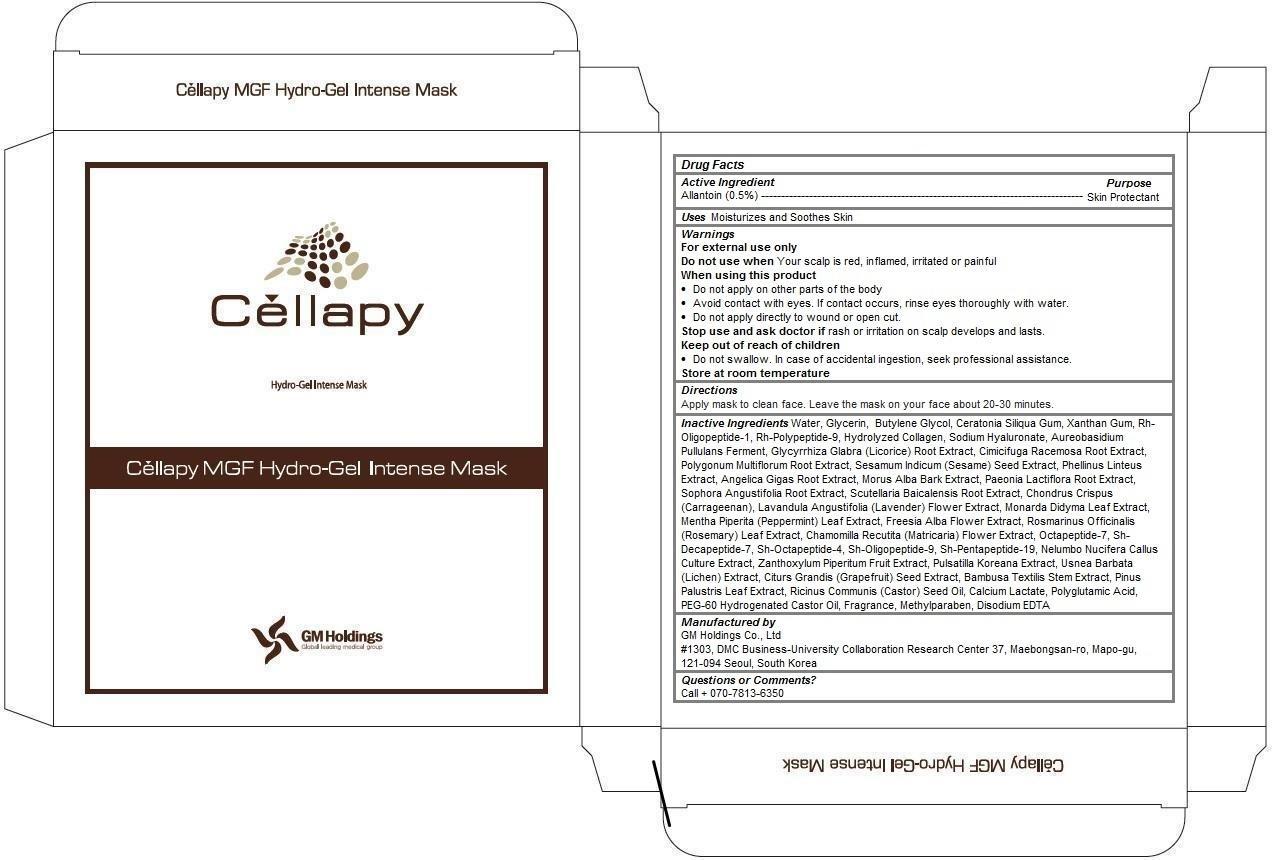 DRUG LABEL: Cellapy MGF Hydro Gel Intense Mask
NDC: 69278-105 | Form: PATCH
Manufacturer: GM Holdings Co., Ltd
Category: otc | Type: HUMAN OTC DRUG LABEL
Date: 20200121

ACTIVE INGREDIENTS: ALLANTOIN 0.5 1/25 g
INACTIVE INGREDIENTS: WATER; GLYCERIN; BUTYLENE GLYCOL; LOCUST BEAN GUM; XANTHAN GUM; NEPIDERMIN; HYALURONATE SODIUM; AUREOBASIDIUM PULLULANS VAR. PULLUTANS; GLYCYRRHIZA GLABRA; BLACK COHOSH; FALLOPIA MULTIFLORA ROOT; SESAME SEED; PHELLINUS LINTEUS WHOLE; ANGELICA GIGAS ROOT; MORUS ALBA BARK; PAEONIA LACTIFLORA ROOT; SOPHORA FLAVESCENS ROOT; SCUTELLARIA BAICALENSIS ROOT; CHONDRUS CRISPUS CARRAGEENAN; LAVANDULA ANGUSTIFOLIA FLOWER; MONARDA DIDYMA LEAF; MENTHA PIPERITA LEAF; FREESIA ALBA FLOWER; ROSEMARY; CHAMOMILE; NELUMBO NUCIFERA FLOWER; ZANTHOXYLUM PIPERITUM FRUIT PULP; PULSATILLA KOREANA ROOT; USNEA BARBATA; CITRUS MAXIMA SEED; BAMBUSA TEXTILIS STEM; PINUS PALUSTRIS LEAF; CASTOR OIL; CALCIUM LACTATE; PEG-60 HYDROGENATED CASTOR OIL; METHYLPARABEN; EDETATE DISODIUM

Cellapy MGF Hydro Gel Intense Mask